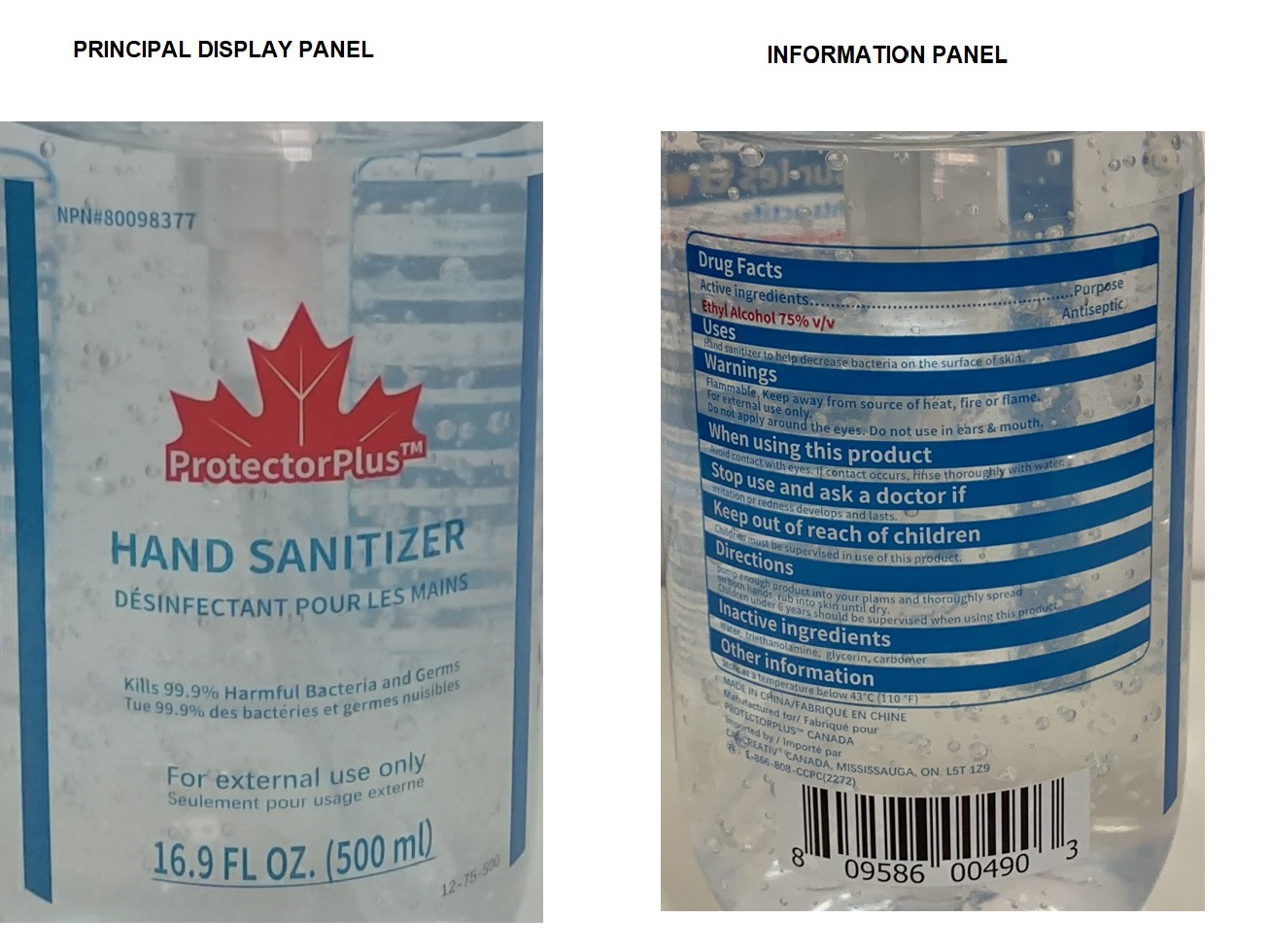 DRUG LABEL: ProtectorPlus HAND SANITIZER
NDC: 78378-888 | Form: GEL
Manufacturer: Cancreativ Packing Corp
Category: otc | Type: HUMAN OTC DRUG LABEL
Date: 20200529

ACTIVE INGREDIENTS: ALCOHOL 75 mL/100 mL
INACTIVE INGREDIENTS: WATER; TROLAMINE; GLYCERIN; CARBOMER HOMOPOLYMER, UNSPECIFIED TYPE

ProtectorPlusTM HAND SANITIZER

Active ingredients

Ethyl Alcohol 75% v/v

Purpose

Antiseptic

Uses

Hand sanitizer to help decrease bacteria on the surface of skin.

Warnings

Flammable, Keep away from source of heat, fire or flame.

For external use only.

Do not apply around the eyes. Do not use in ears & mouth.

When using this product Avoid contact with eyes. If contact occurs, rinse thoroughly with water.

Stop use and ask a doctor if irritation or redness develops and lasts.

Keep out of reach of children. Children must be supervised in use of this product.

Directions

pump enough product into your palms and thoroughly spread on both hands, rub into skin until dry.

Children under 6 years should be supervised when using this product.

Other information

Store at a temperature below 43°C (110° F)

Inactive ingredients

water, triethanolamine, glycerin, carbomer

DÉSINFECTANT POUR LES MAINS

Kills 99.9% Harmful Bacteria and Germs

Tue 99.9% des bactéries et germs nuisibles

For external use only

Seulement pour usage externe

MADE IN CHINA/ FABRIQUE EN CHINE

Manufactured for/ Fabriqué pour

PROTECTORPLUS TM CANADA

Imported by / Importé par

CANCREATIV CANADA, MISSISSAUGA, ON L5T 1Z9

1-866-808-CCPC(2272)